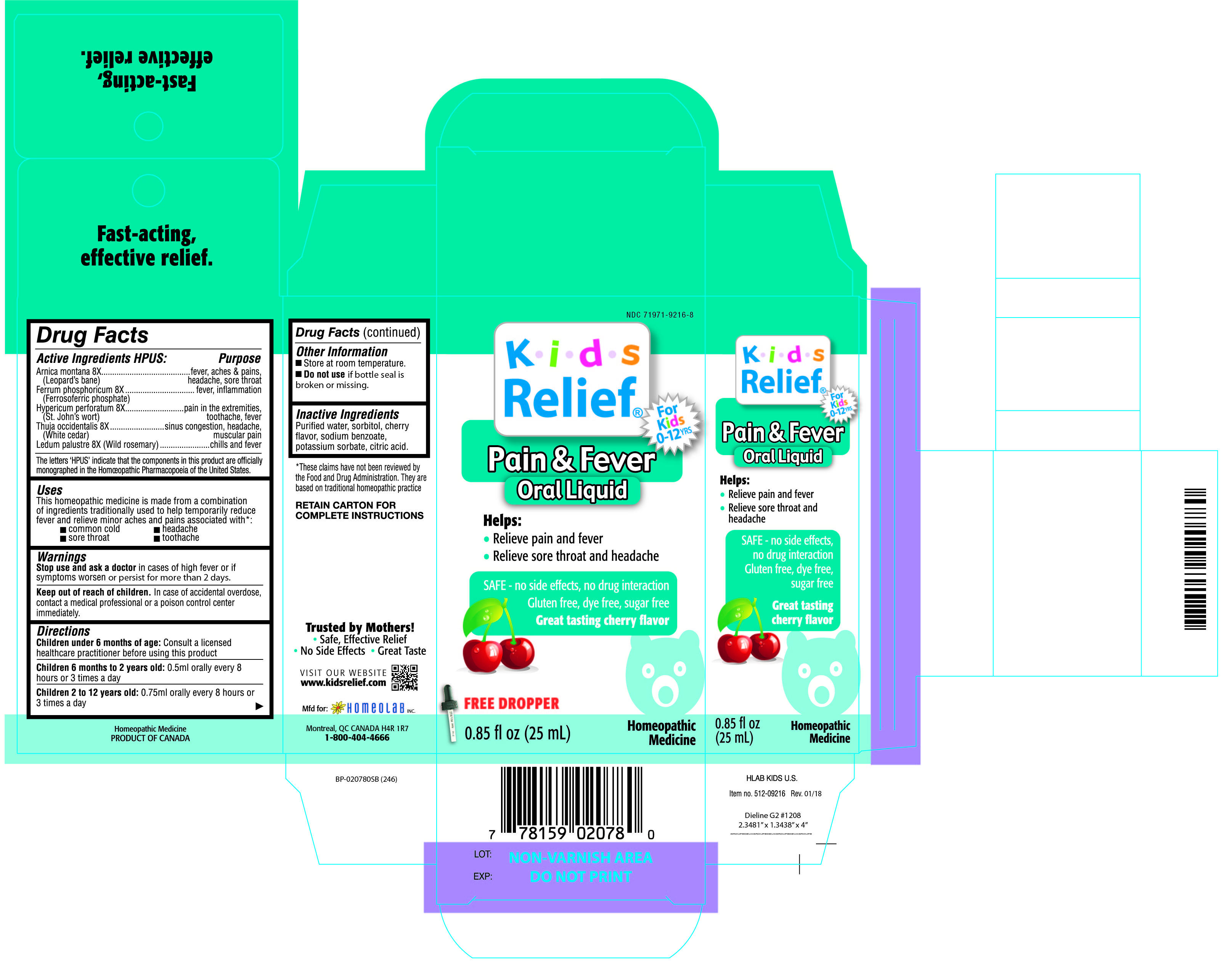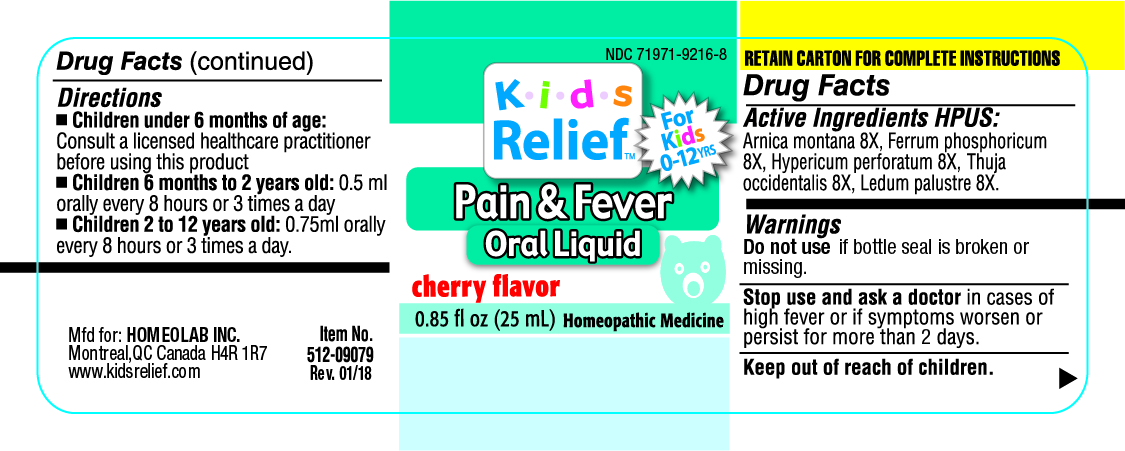 DRUG LABEL: Kids Relief
NDC: 71971-9216 | Form: LIQUID
Manufacturer: Homeolab International (Canada) inc
Category: homeopathic | Type: HUMAN OTC DRUG LABEL
Date: 20190716

ACTIVE INGREDIENTS: ARNICA MONTANA 8 [hp_X]/25 mL; FERRUM PHOSPHORICUM 8 [hp_X]/25 mL; HYPERICUM PERFORATUM 8 [hp_X]/25 mL; THUJA OCCIDENTALIS LEAFY TWIG 8 [hp_X]/25 mL; RHODODENDRON TOMENTOSUM LEAFY TWIG 8 [hp_X]/25 mL
INACTIVE INGREDIENTS: WATER; SORBITOL; SODIUM BENZOATE; POTASSIUM SORBATE; CITRIC ACID ACETATE

Active Ingredients HPUS:

Arnica montana 8X

(Leopard's bane)

Ferrum phosphoricum 8X

(Ferrosoferric phosphate)

Hypericum perforatum 8X

(St. John's wort)

Thuja occidentalis 8X

(White cedar)

Ledum palustre 8X (Wild rosemary)

The letters 'HPUS' indicate that the component in this product is officially

monographed in the Homeopathic Pharmacopoeia of the United States.

Purpose

Arnica montana 8X.............................................fever, aches & pains, headache, sore throat

(Leopard's bane)

Ferrum phosphoricum 8X.....................................fever, inflammation

(Ferrosoferric phosphate)

Hypericum perforatum 8X....................................pain in the extremeties, toothache, fever

(St. John's wort)

Thuja occidentalis 8X..........................................sinus congestion, headache, muscular pain

(White cedar)

Ledum palustre 8X (Wild rosemary).....................chills and fever

Uses

This homeopathic medicine is made from a combination of

ingredients traditionally used to help temporarily reduce

fever and relieve minor aches and pains associated with:

•common cold •headache

•sore throat •toothache

Warnings

Stop use and ask a doctor in cases of high fever or if

symptoms worsen or persist for mroe than 2 days.

Keep out of reach of children. In case of accidental overdose,

contact a medical professional or a poison control center

immediately.

Directions

Children under 6 months of age: Consult a licensed healthcare

practitioner before using this product

Children under 6 months to 2 years old: 0.5 ml orally every 8 hours

or 3 times a day

Children 2 to 12 years old: 0.75 ml orally every 8 hours or

3 times a day

Other information

•Store at room temperature

•Do not use if bottle seal

is broken or missing.

Inactive Ingredients

Purified water, sorbitol, cherry

flavor, sodium benzoate,

potassium sorbate, citric acid.